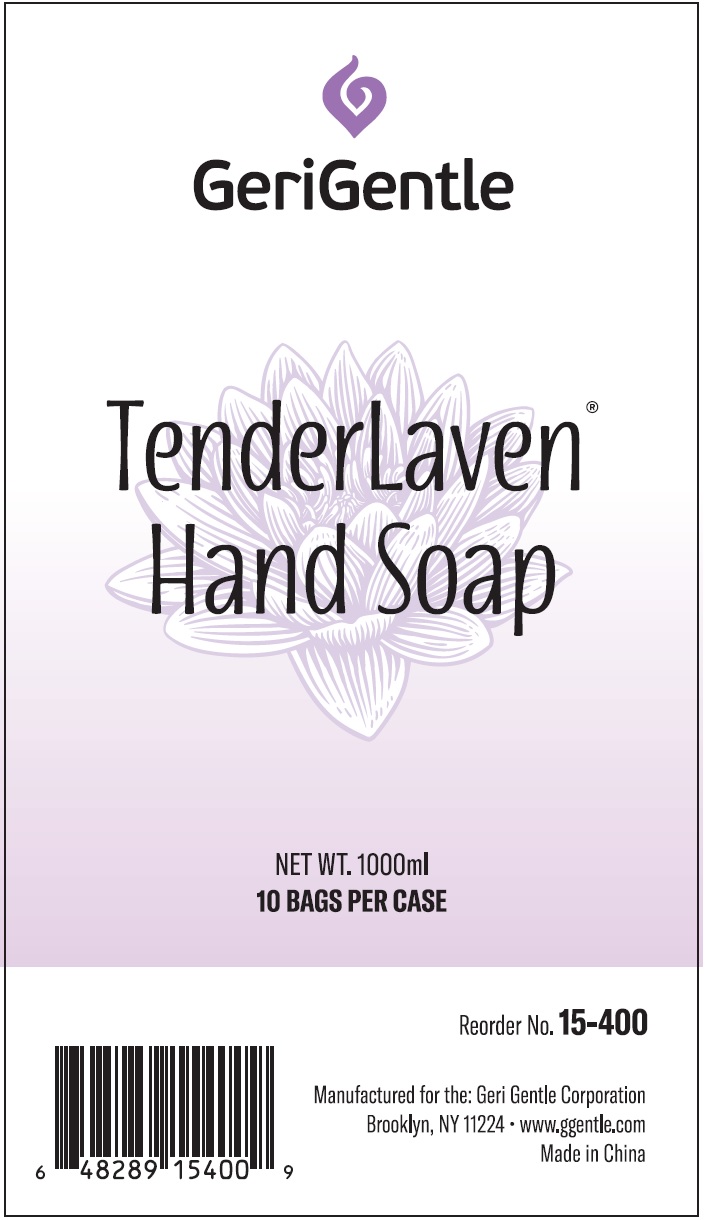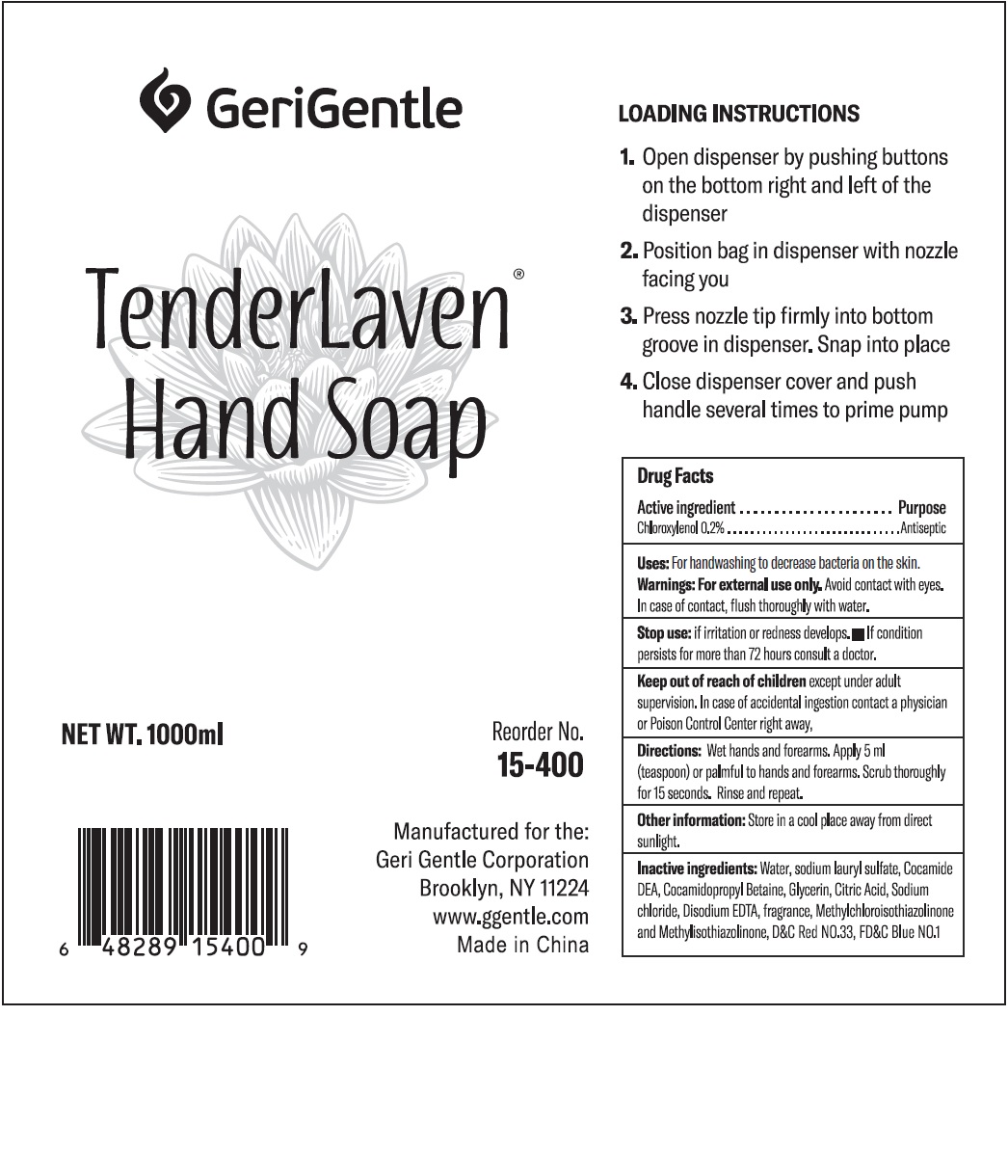 DRUG LABEL: TenderLaven Hand
NDC: 69771-006 | Form: GEL
Manufacturer: Geri-Gentle Corporation
Category: otc | Type: HUMAN OTC DRUG LABEL
Date: 20231110

ACTIVE INGREDIENTS: CHLOROXYLENOL 2 mg/1 mL
INACTIVE INGREDIENTS: WATER; SODIUM LAURYL SULFATE; COCO DIETHANOLAMIDE; COCAMIDOPROPYL BETAINE; GLYCERIN; CITRIC ACID MONOHYDRATE; SODIUM CHLORIDE; EDETATE DISODIUM ANHYDROUS; METHYLCHLOROISOTHIAZOLINONE; METHYLISOTHIAZOLINONE; D&C RED NO. 33; FD&C BLUE NO. 1

TenderLaven Hand Soap

Active ingredient

Chloroxylenol 0.2%

Purpose

Antiseptic

Uses:

For handwashing to decrease bacteria on the skin.

Warnings:

Avoid contact with eyes. In case of contact, flush thoroughly with water. For external use only.

Stop use:

if irritation or redness develops.

If condition persists for more than 72 hours consult a doctor.

Keep out of reach of children

except under adult supervision. In case of accidental ingestion contact a physician or Poison Control Center right away.

Directions:

Wet hands and forearms. Apply 5 ml (teaspoon) or palmful to hands and forearms. Scrub thoroughly for 15 seconds. Rinse and repeat.

Other information:

Store in a cool place away from direct sunlight.

Inactive ingredients:

Water, sodium lauryl sulfate, Cocamide DEA, Cocamidopropyl Betaine, Glycerin, Citric Acid, Sodium chloride, Disodium EDTA, fragrance, Methylchloroisothiazolinone and Methylisothiazolinone, D&C Red NO.33, FD&C Blue NO.1